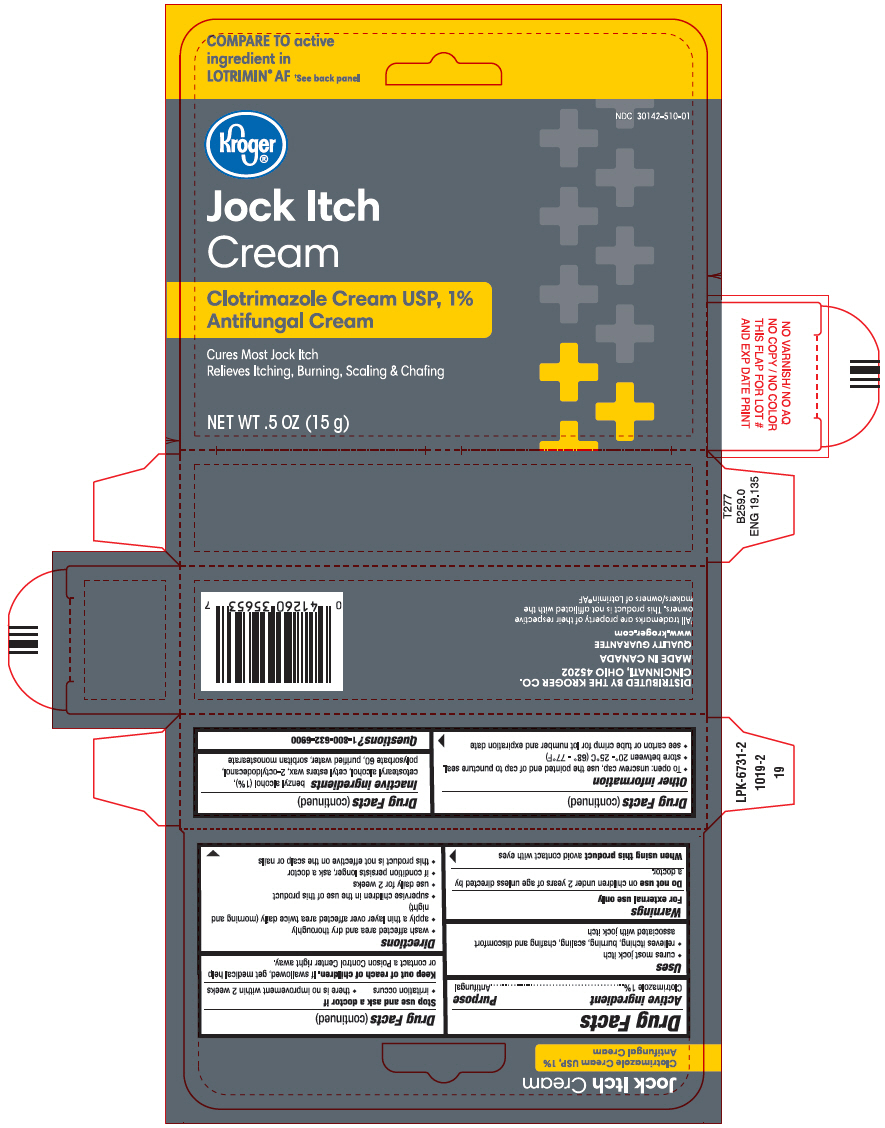 DRUG LABEL: Kroger

NDC: 30142-510 | Form: CREAM
Manufacturer: Kroger Company
Category: otc | Type: HUMAN OTC DRUG LABEL
Date: 20250708

ACTIVE INGREDIENTS: CLOTRIMAZOLE 10 mg/1 g
INACTIVE INGREDIENTS: BENZYL ALCOHOL; CETOSTEARYL ALCOHOL; CETYL ESTERS WAX; OCTYLDODECANOL; POLYSORBATE 60; WATER; SORBITAN MONOSTEARATE

Kroger®
Jock Itch

Drug Facts

Active ingredient

Clotrimazole 1%

Purpose

Antifungal

Uses

- cures most jock itch
- relieves itching, burning, scaling, chafing and discomfort associated with jock itch

Warnings

For external use only

DO NOT USE

Do not useon children under 2 years of age unless directed by a doctor.

When using this productavoid contact with eyes

Stop use and ask a doctor if

- irritation occurs
- there is no improvement within 2 weeks

Keep out of reach of children.If swallowed, get medical help or contact a Poison Control Center right away.

Directions

- wash affected area and dry thoroughly
- apply a thin layer over affected area twice daily (morning and night)
- supervise children in the use of this product
- use daily for 2 weeks
- if condition persists longer, ask a doctor
- this product is not effective on the scalp or nails

Other information

- To open: unscrew cap, use the pointed end of cap to puncture seal.
- store between 20° - 25°C (68° - 77°F)
- see carton or tube crimp for lot number and expiration date

Inactive ingredients

benzyl alcohol (1%), cetostearyl alcohol, cetyl esters wax, 2-octyldodecanol, polysorbate 60, purified water, sorbitan monostearate

Questions?

1-800-632-6900

DISTRIBUTED BY THE KROGER CO.
CINCINNATI, OHIO 45202

PRINCIPAL DISPLAY PANEL - 15 g Tube Carton

COMPARE TO active
ingredient in
LOTRIMIN®AF†See back panel

NDC 30142-510-01

Kroger®

Jock Itch
Cream

Clotrimazole Cream USP, 1%
Antifungal Cream

Cures Most Jock Itch
Relieves Itching, Burning, Scaling & Chafing

NET WT .5 OZ (15 g)